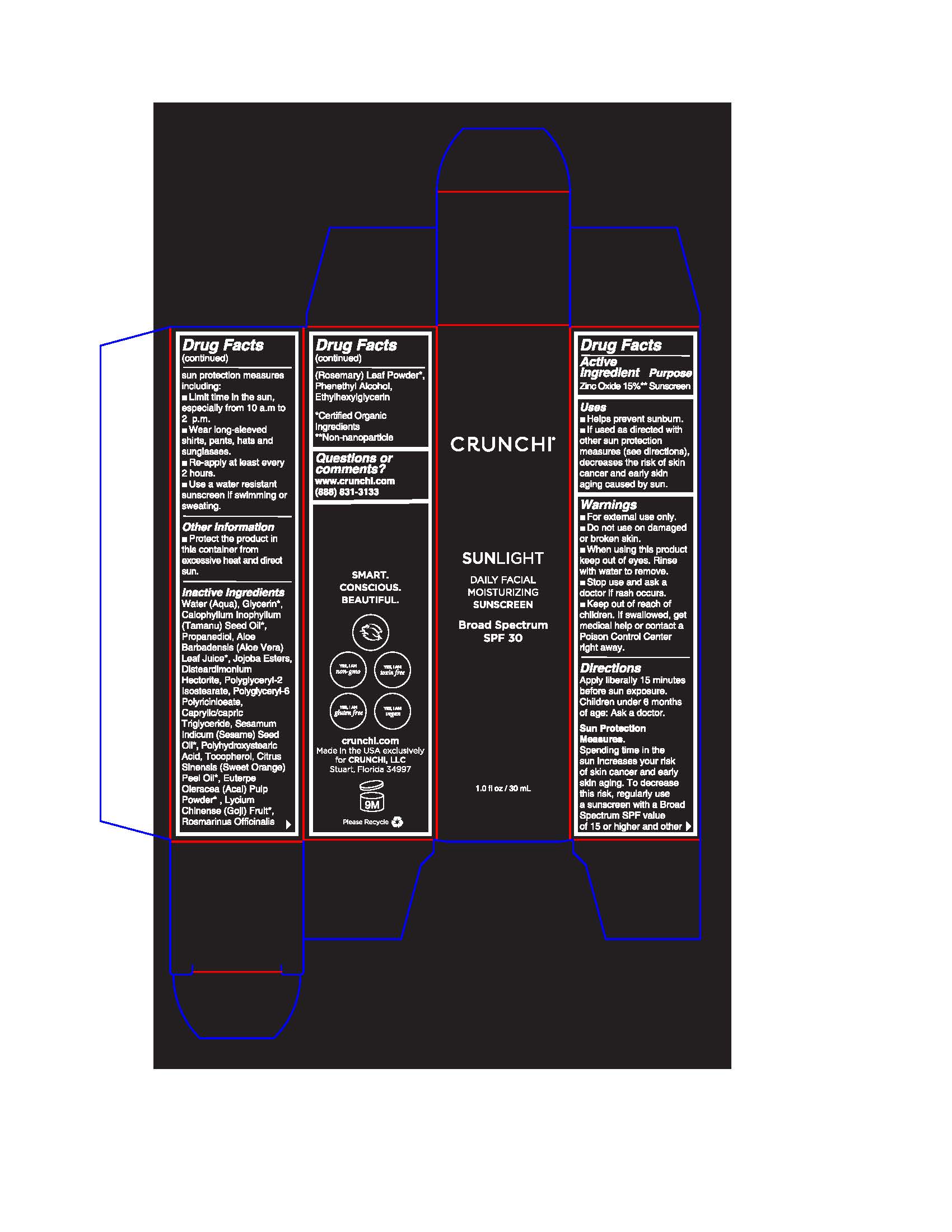 DRUG LABEL: Sunlight Daily Facial Moisturizing Sunscreen
NDC: 72444-0130 | Form: LOTION
Manufacturer: Crunchi LLC
Category: otc | Type: HUMAN OTC DRUG LABEL
Date: 20201120

ACTIVE INGREDIENTS: ZINC OXIDE 4.5 g/30 mL
INACTIVE INGREDIENTS: WATER

Crunchi

Active Ingredient

Zinc Oxide 15%** Sunscreen

Uses

- Helps prevent sunburn.
- If used as directed with other sun protection measures (see directions), decreases the risk of skin cancer and early skin aging caused by the sun.

Warnings

- For external use only.
- Do not use on damaged or broken skin.
- When using this product keep out of eyes. Rinse with water to remove.
- Stop use and ask a doctor if rash occurs.
- Keep out of reach of children. If swallowed, get medical help or contact a Poison Control Center right away.

Directions

Apply liberally 15 minutes before sun exposure.

Children under 6 months of age: Ask a doctor.

Sun Protection Measures.

Spending time in the sun increases your risk of skin cancer and early skin aging. To decrease this risk, regularly use a sunscreen with a Broad Spectrum SPF value of 15 or higher and other sun protection measures including:

- Limit time in the sun, especially from 10 a.m. to 2 p.m.
- Wear long-sleeved shirts, pants, hats and sunglasses.
- Re-apply at least every 2 hours.
- Use a water resistant sunscreen if swimming or sweating.

Other Information

- Protect the product in this container from excessive heat and direct sun.

Inactive Ingredients

Water (Aqua), Glycerin*, Calophyllum inophyllum (Tamanu) Seed Oil*, Propsnediol, Aloe Barbadensis (Aloe Vera) Leaf Juice*, Jojoba Esters, Disteardimonium Hectorite, Polyglyceryl-2 Isostearate, Polyglyceryl-6 Polyricinloeate, Caprylic/capric Triglyceride, Sesamum Indicum (Sesame) Seed Oil*, Polyhydroxystearic Acid, Tocopherol, Citrus Sinsnsis (Sweet Oralge) Peel Oil*, Euterpe Oleracea (Acai) Pulp Powder*, Lycium Chinense (Goji) Fruit*, Rosmarinus Officinalis (Rosemary) Leaf Powder*, Phenethyl Alcohol, Ethylhexylglycerin

*Certified Organic Ingredients

**Non-nanoparticle

Questions or comments?

www.crunchi.com

(888) 831-3133